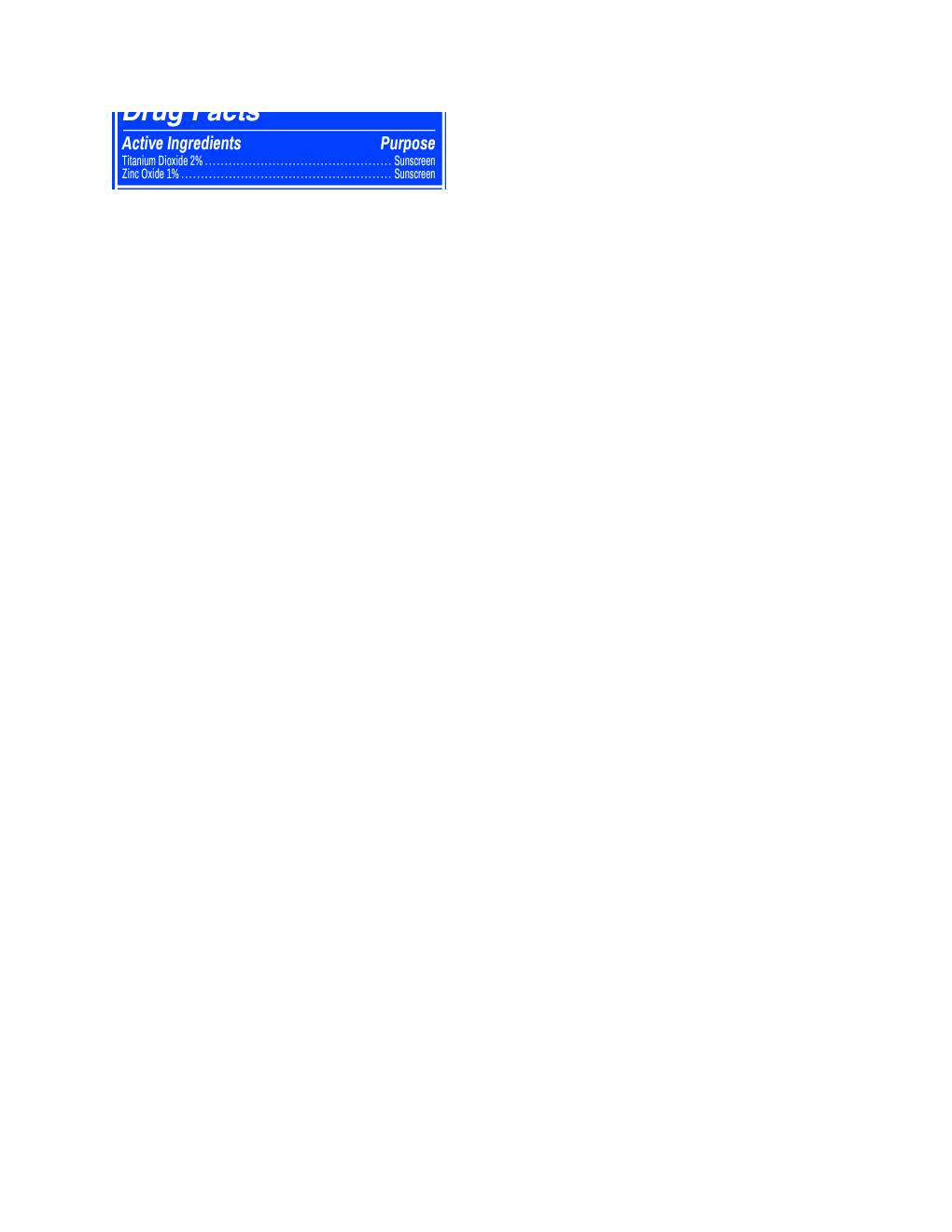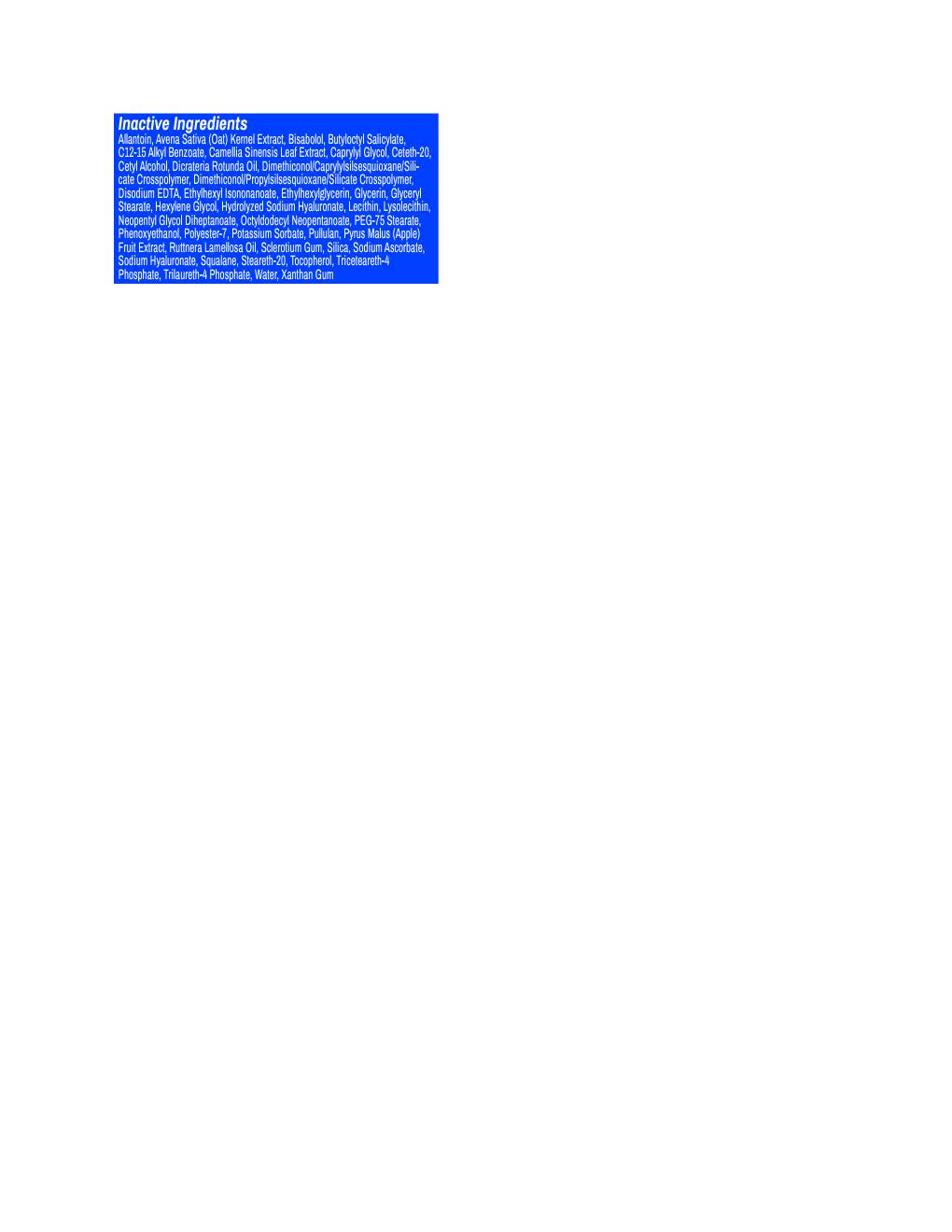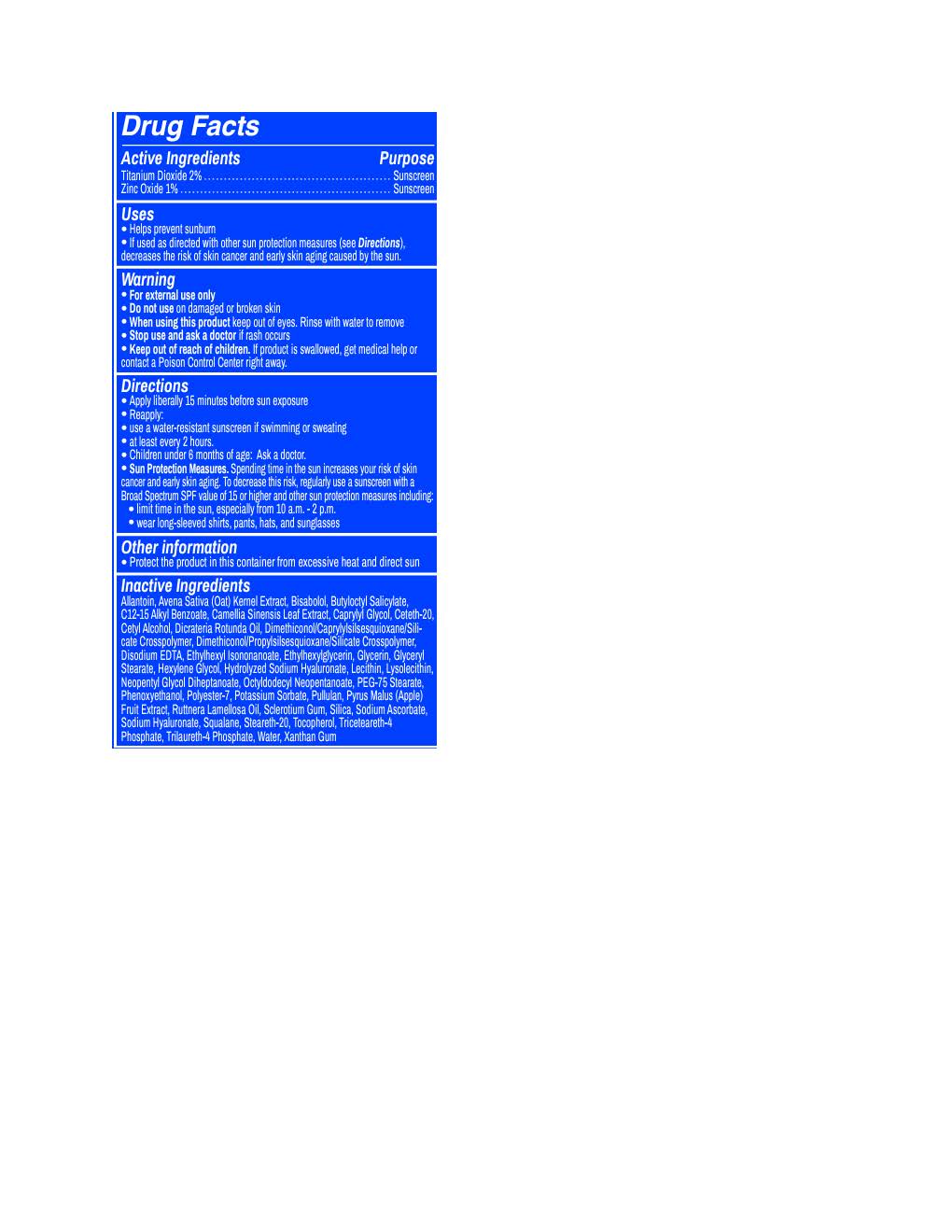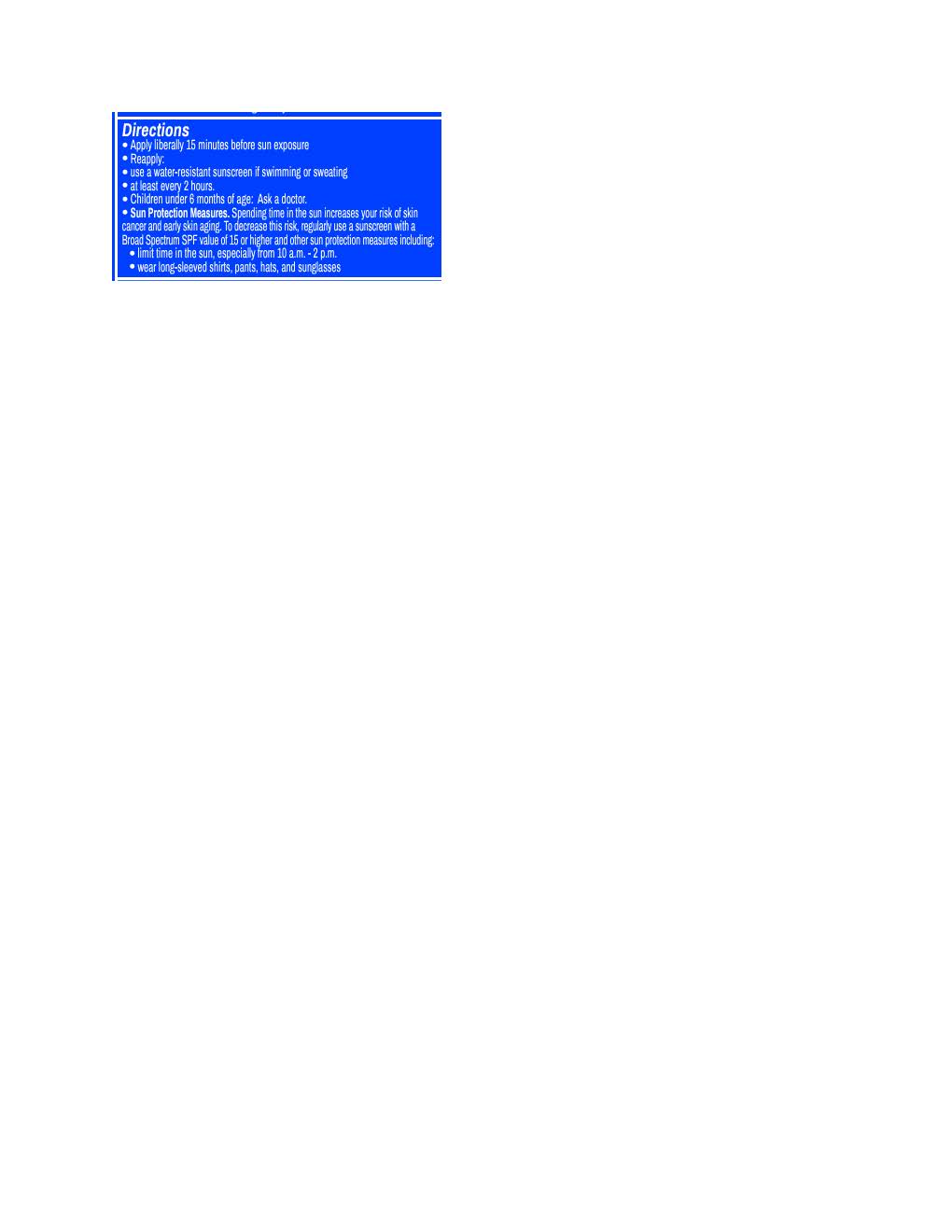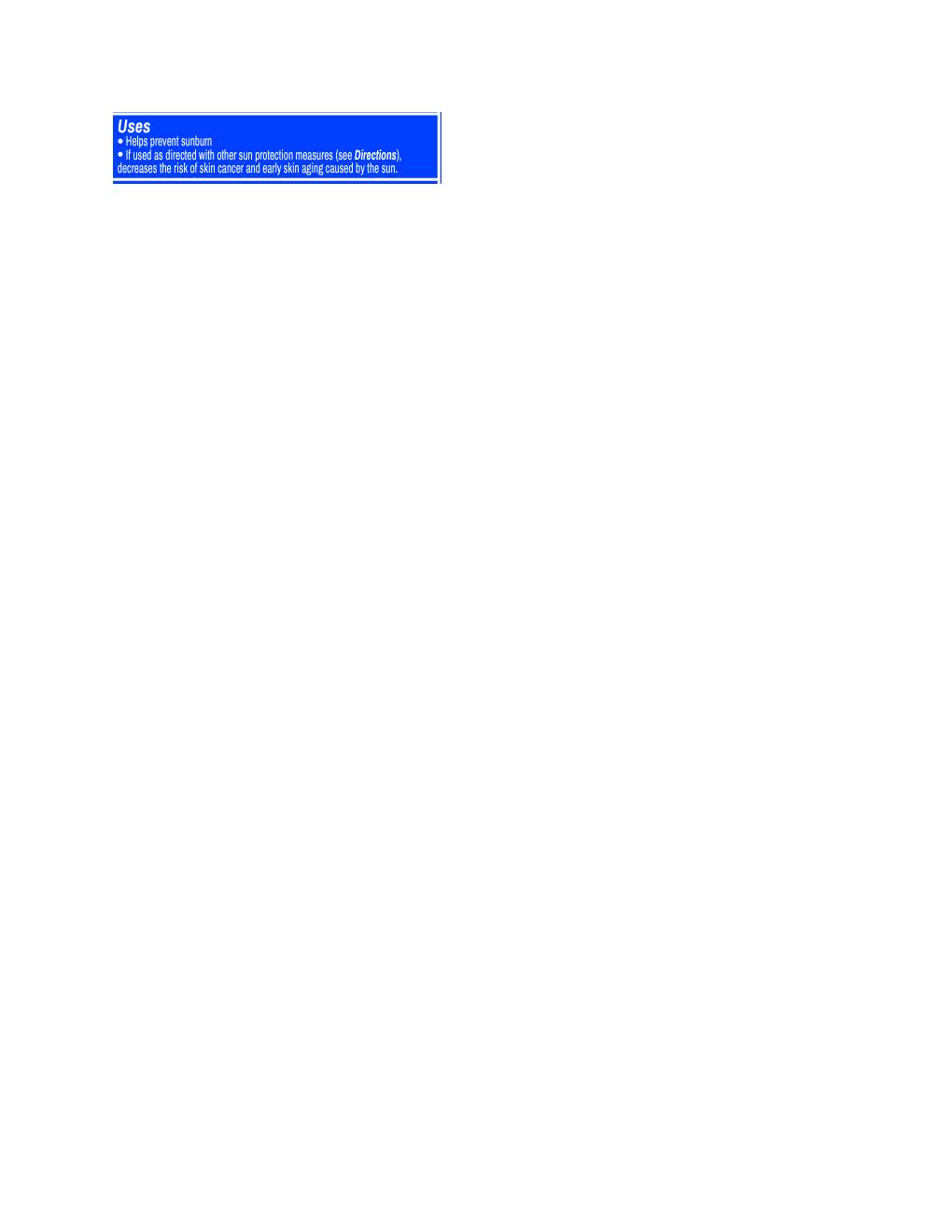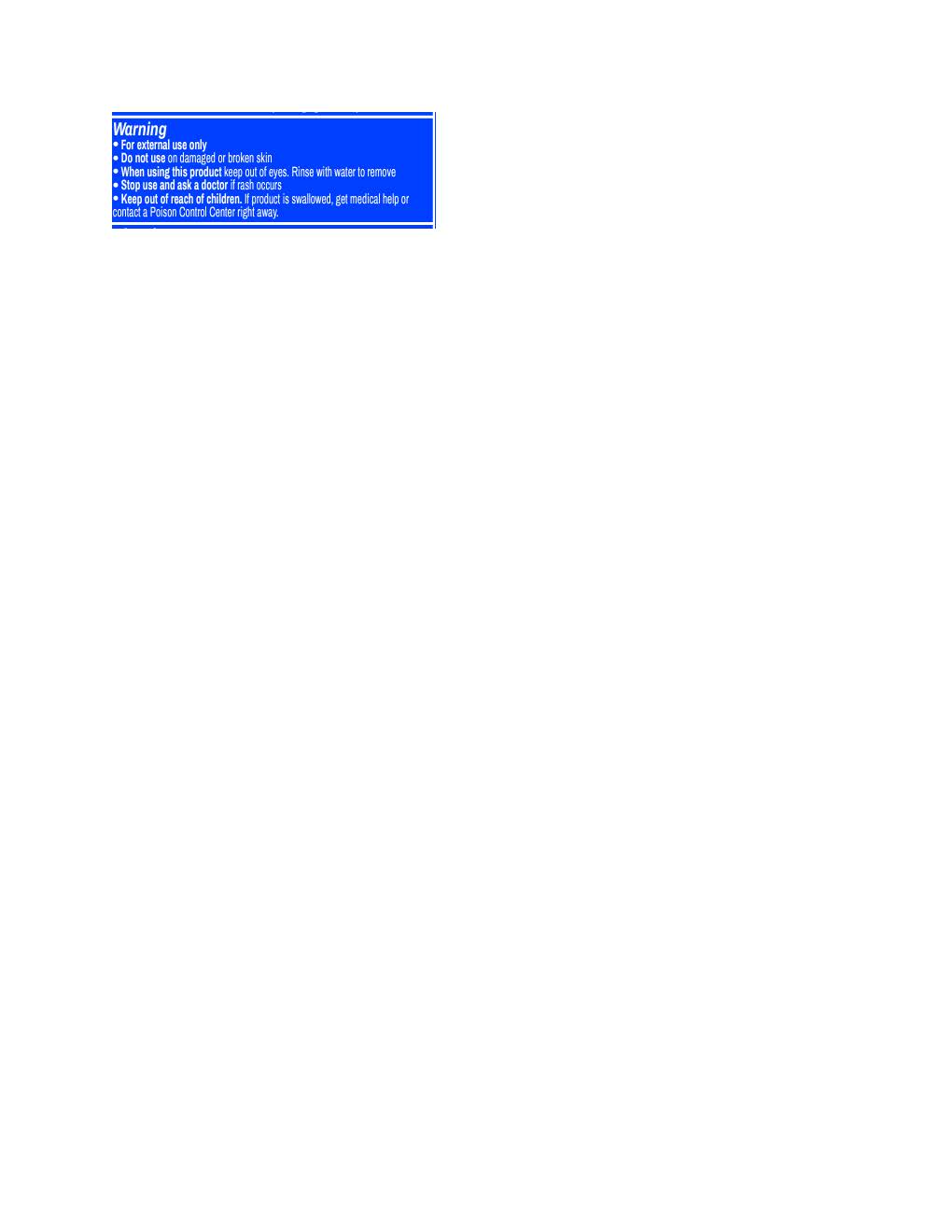 DRUG LABEL: Huey Daily Mineral
NDC: 83599-391 | Form: LOTION
Manufacturer: Huey
Category: otc | Type: HUMAN OTC DRUG LABEL
Date: 20251114

ACTIVE INGREDIENTS: ZINC OXIDE 9.7 mg/1 mL; TITANIUM DIOXIDE 19.4 mg/1 mL
INACTIVE INGREDIENTS: GLYCERYL STEARATE SE; ALKYL (C12-15) BENZOATE; ALLANTOIN; CAPRYLYL GLYCOL; AVENA SATIVA WHOLE; XANTHAN GUM; DICRATERIA ROTUNDA OIL; DISODIUM EDTA-COPPER; CAMELLIA SINENSIS WHOLE; TRICETEARETH-4 PHOSPHATE; PULLULAN; STEARETH-20; HEXYLENE GLYCOL; TRILAURETH-4 PHOSPHATE; SODIUM ASCORBATE; OCTYLDODECYL NEOPENTANOATE; CETYL ALCOHOL; SQUALANE; PEG-75 STEARATE; PHENOXYETHANOL; .ALPHA.-BISABOLOL, (+)-; ETHYLHEXYLGLYCERIN; DIMETHICONOL/PROPYLSILSESQUIOXANE/SILICATE CROSSPOLYMER (450000000 MW); LECITHIN, SOYBEAN; SILICON DIOXIDE; ETHYLHEXYL ISONONANOATE; CETETH-20; POTASSIUM SORBATE; TOCOPHEROL; RUTTNERA LAMELLOSA OIL; BUTYLOCTYL SALICYLATE; POLYESTER-7; GLYCERIN; NEOPENTYL GLYCOL DIHEPTANOATE

Huey Daily Mineral